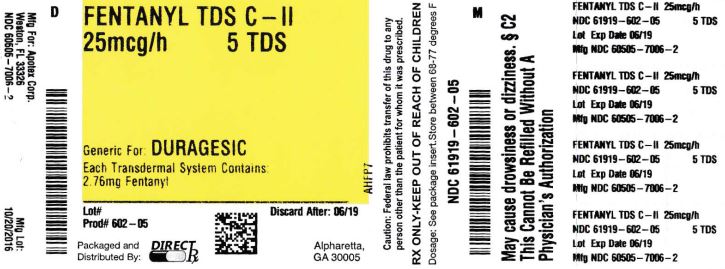 DRUG LABEL: FENTANYL
NDC: 61919-602 | Form: PATCH, EXTENDED RELEASE
Manufacturer: DirectRX
Category: prescription | Type: HUMAN PRESCRIPTION DRUG LABEL
Date: 20200120
DEA Schedule: CII

ACTIVE INGREDIENTS: FENTANYL 25 ug/1 h
INACTIVE INGREDIENTS: ISOPROPYL MYRISTATE; OCTYLDODECANOL; POLYBUTENE (1400 MW); POLYISOBUTYLENE (800000 MW)

FENTANYL

BOXED WARNING SECTION

- WARNING: ADDICTION, ABUSE, AND MISUSE; LIFE-THREATENING, RESPIRATORY DEPRESSION, ACCIDENTAL EXPOSURE, NEONATAL OPIOID WITHDRAWAL SYNDROME; CYTOCHROME P450 3A4 INTERACTION; and EXPOSURE TO HEAT
  Addiction, Abuse, and Misuse
  Fentanyl transdermal system exposes patients and other users to the risks of opioid addiction, abuse, and misuse, which can lead to overdose and death. Assess each patient’s risk prior to prescribing Fentanyl transdermal system, and monitor all patients regularly for the development of these behaviors or conditions [see Warnings and Precautions (5.1)].
  Life-threatening Respiratory Depression
  Serious, life-threatening, or fatal respiratory depression may occur with use of fentanyl transdermal system, even when used as recommended. Monitor for respiratory depression, especially during initiation of fentanyl transdermal system or following a dose increase. Because of the risk of respiratory depression, fentanyl transdermal system is contraindicated for use as an as-needed analgesic, in non-opioid tolerant patients, in acute pain, and in postoperative pain [see Contraindications (4) and Warnings and Precautions (5.2)].
  Accidental Exposure
  Deaths due to a fatal overdose of fentanyl have occurred when children and adults were accidentally exposed to fentanyl transdermal system. Strict adherence to the recommended handling and disposal instructions is of the utmost importance to prevent accidental exposure [see Warnings and Precautions (5.3)].
  Neonatal Opioid Withdrawal Syndrome
  Prolonged use of fentanyl transdermal system during pregnancy can result in neonatal opioid withdrawal syndrome, which may be life-threatening if not recognized and treated, and requires management according to protocols developed by neonatology experts. If opioid use is required for a prolonged period in a pregnant woman, advise the patient of the risk of neonatal opioid withdrawal syndrome and ensure that appropriate treatment will be available [see Warnings and Precautions (5.4)].
  Cytochrome P450 3A4 Interaction
  The concomitant use of fentanyl transdermal system with all cytochrome P450 3A4 inhibitors may result in an increase in fentanyl plasma concentrations, which could increase or prolong adverse drug effects and may cause potentially fatal respiratory depression. In addition, discontinuation of a concomitantly used cytochrome P450 3A4 inducer may result in an increase in fentanyl plasma concentration. Monitor patients receiving fentanyl transdermal system and any CYP3A4 inhibitor or inducer [see Warnings and Precautions (5.10), and Clinical Pharmacology (12.3)].
  Exposure To Heat
  Exposure of the fentanyl transdermal system application site and surrounding area to direct external heat sources, such as heating pads or electric blankets, heat or tanning lamps, sunbathing, hot baths, saunas, hot tubs, and heated water beds may increase fentanyl absorption and has resulted in fatal overdose of fentanyl and death [see Warnings and Precautions (5.11)]. Patients wearing fentanyl transdermal systems who develop fever or increased core body temperature due to strenuous exertion are also at risk for increased fentanyl exposure and may require an adjustment in the dose of fentanyl transdermal system to avoid overdose and death [see Warnings and Precautions (5.12)].

INDICATIONS & USAGE SECTION

- Fentanyl transdermal system is indicated for the management of pain in opioid-tolerant patients, severe enough to require daily, around-the-clock, long- term opioid treatment and for which alternative treatment options are inadequate.
  Patients considered opioid-tolerant are those who are taking, for one week or longer, at least 60 mg of morphine daily, or at least 30 mg of oral oxycodone daily, or at least 8 mg of oral hydromorphone daily, or an equianalgesic dose of another opioid.
  Limitations of Use
  - Because of the risks of addiction, abuse, and misuse with opioids, even at recommended doses, and because of the greater risks of overdose and death with extended-release opioid formulations, reserve fentanyl transdermal system for use in patients for whom alternative treatment options (e.g., non-opioid analgesics or immediate-release opioids) are ineffective, not tolerated, or would be otherwise inadequate to provide sufficient management of pain.

DOSAGE & ADMINISTRATION SECTION

- 2.1 Initial Dosing
  Fentanyl transdermal system should be prescribed only by healthcare professionals who are knowledgeable in the use of potent opioids for the management of chronic pain.
  Due to the risk of respiratory depression, fentanyl transdermal system is only indicated for use in patients who are already opioid-tolerant. Discontinue or taper all other extended-release opioids when beginning fentanyl transdermal system therapy. As fentanyl transdermal system is only for use in opioid-tolerant patients, do not begin any patient on fentanyl transdermal system as the first opioid.
  Patients considered opioid-tolerant are those who are taking at least 60 mg of morphine daily, or at least 30 mg of oral oxycodone daily, or at least 8 mg of oral hydromorphone daily or an equianalgesic dose of another opioid for a week or longer.
  Initiate the dosing regimen for each patient individually, taking into account the patient's prior analgesic treatment experience and risk factors for addiction, abuse, and misuse [see Warnings and Precautions (5.1)]. Monitor patients closely for respiratory depression, especially within the first 24-72 hours of initiating therapy with fentanyl transdermal system when serum concentrations from the initial patch will peak [see Warnings and Precautions (5.2)].
  The recommended starting dose when converting from other opioids to fentanyl transdermal system is intended to minimize the potential for overdosing patients with the first dose.
  Discontinue all other around-the-clock opioid drugs when fentanyl transdermal system therapy is initiated.
  While there are useful tables of opioid equivalents readily available, there is substantial inter-patient variability in the relative potency of different opioid drugs and products. As such, it is preferable to underestimate a patient’s 24-hour fentanyl requirements and provide rescue medication (e.g., immediate-release opioid) than to overestimate the 24-hour fentanyl requirements which could result in adverse reactions. In a fentanyl transdermal system clinical trial, patients were converted from their prior opioid to fentanyl transdermal system using Table 1 as a guide for the initial fentanyl transdermal system dose.
  Consider the following when using the information in Table 1:
  - This is not a table of equianalgesic doses.
  - The conversion doses in this table are only for the conversion from one of the listed oral or parenteral opioid analgesics to fentanyl transdermal system.
  - The table cannot be used to convert from fentanyl to another opioid. Doing so will result in an overestimation of the dose of the new opioid and may result in fatal overdose.
  To convert patients from oral or parenteral opioids to fentanyl transdermal system, use Table 1. Do not use Table 1 to convert from fentanyl transdermal system to other therapies because this conversion to fentanyl transdermal system is conservative and will overestimate the dose of the new agent.
  Table 11: DOSE CONVERSION TO FENTANYL TRANSDERMAL SYSTEM
  Current Analgesic | Daily Dosage (mg/day)
  Oral morphine | 60-134 | 135-224 | 225-314 | 315-404
  Intramuscular or Intravenous morphine | 10-22 | 23-37 | 38-52 | 53-67
  Oral oxycodone | 30-67 | 67.5-112 | 112.5-157 | 157.5-202
  Oral codeine | 150-447
  Oral hydromorphone | 8-17 | 17.1-28 | 28.1-39 | 39.1-51
  Intravenous hydromorphone | 1.5-3.4 | 3.5-5.6 | 5.7-7.9 | 8-10
  Intramuscular meperidine | 75-165 | 166-278 | 279-390 | 391-503
  Oral methadone | 20-44 | 45-74 | 75-104 | 105-134
   | ↓ | ↓ | ↓ | ↓
  Recommended Fentanyl Transdermal System Dose | 25 mcg/hour | 50 mcg/hour | 75 mcg/hour | 100 mcg/hour
  Alternatively, for adult and pediatric patients taking opioids or doses not listed in Table 1, use the conversion methodology outlined above with Table 2
  1 Table 1 should not be used to convert from fentanyl transdermal system to other therapies because this conversion to fentanyl transdermal system is conservative. Use of Table 1 for conversion to other analgesic therapies can overestimate the dose of the new agent. Overdosage of the new analgesic agent is possible [see Dosage and Administration (2.3)].
  Alternatively, for adult and pediatric patients taking opioids or doses not listed in Table 1, use the following methodology:
  1. Calculate the previous 24-hour analgesic requirement.
  2. Convert this amount to the equianalgesic oral morphine dose using a reliable reference.
  Refer to Table 2 for the range of 24-hour oral morphine doses that are recommended for conversion to each fentanyl transdermal system dose. Use this table to find the calculated 24-hour morphine dose and the corresponding fentanyl transdermal system dose. Initiate fentanyl transdermal system treatment using the recommended dose and titrate patients upwards (no more frequently than 3 days after the initial dose and every 6 days thereafter) until analgesic efficacy is attained.
  3. Do not use Table 2 to convert from fentanyl transdermal system to other therapies because this conversion to fentanyl transdermal system is conservative and will overestimate the dose of the new agent.
  Table 21: RECOMMENDED INITIAL FENTANYL TRANSDERMAL SYSTEM DOSE BASED UPON DAILY ORAL MORPHINE DOSE
  Oral 24-hour Morphine (mg/day) | Fentanyl Transdermal System Dose (mcg/hour)
  60-134 | 25
  135-224 | 50
  225-314 | 75
  315-404 | 100
  405-494 | 125
  495-584 | 150
  585-674 | 175
  675-764 | 200
  765-854 | 225
  855-944 | 250
  945-1034 | 275
  1035-1124 | 300
  NOTE: In clinical trials, these ranges of daily oral morphine doses were used as a basis for conversion to fentanyl transdermal system.
  1 Table 2 should not be used to convert from fentanyl transdermal system to other therapies because this conversion to fentanyl transdermal system is conservative. Use of Table 2 for conversion to other analgesic therapies can overestimate the dose of the new agent. Overdosage of the new analgesic agent is possible [see Dosage and Administration (2.5)].
  For delivery rates in excess of 100 mcg/hour, multiple systems may be used.
  Hepatic Impairment
  Avoid the use of fentanyl transdermal system in patients with severe hepatic impairment. In patients with mild to moderate hepatic impairment, start with one half of the usual dosage of fentanyl transdermal system. Closely monitor for signs of sedation and respiratory depression, including at each dosage increase [see Warnings and Precautions (5.14), Use in Specific Populations (8.6) and Clinical Pharmacology (12.3)].
  Renal Impairment
  Avoid the use of fentanyl transdermal system in patients with severe renal impairment. In patients with mild to moderate renal impairment, start with one half of the usual dosage of fentanyl transdermal system. Closely monitor for signs of sedation and respiratory depression, including at each dosage increase [see Warnings and Precautions (5.15), Use in Specific Populations (8.7) and Clinical Pharmacology (12.3)].
  2.2 Titration and Maintenance of Therapy
  Individually titrate fentanyl transdermal system to a dose that provides adequate analgesia and minimizes adverse reactions. Continually reevaluate patients receiving fentanyl transdermal system to assess the maintenance of pain control and the relative incidence of adverse reactions, as well as monitoring for the development of addiction, abuse, or misuse. Frequent communication is important among the prescriber, other members of the healthcare team, the patient, and the caregiver/family during periods of changing analgesic requirements, including initial titration. During chronic therapy, periodically reassess the continued need for opioid analgesics.
  The dosing interval for fentanyl transdermal system is 72 hours. Do not increase the fentanyl transdermal system dose for the first time until at least 3 days after the initial application. Titrate the dose based on the daily dose of supplemental opioid analgesics required by the patient on the second or third day of the initial application.
  It may take up to 6 days for fentanyl levels to reach equilibrium on a new dose [see Clinical Pharmacology (12.3)]. Therefore, evaluate patients for further titration after no less than two 3-day applications before any further increase in dosage is made.
  Base dosage increments on the daily dosage of supplementary opioids, using the ratio of 45 mg/24 hours of oral morphine to a 12 mcg/hour increase in fentanyl transdermal system dose.
  If unacceptable opioid-related adverse reactions are observed, the subsequent doses may be reduced. Adjust the dose to obtain an appropriate balance between management of pain and opioid-related adverse reactions.
  A small proportion of adult patients may not achieve adequate analgesia using a 72-hour dosing interval and may require systems to be applied at 48 hours rather than at 72 hours, only if adequate pain control cannot be achieved using a 72-hour regimen. An increase in the fentanyl transdermal system dose should be evaluated before changing dosing intervals in order to maintain patients on a 72-hour regimen.
  Dosing intervals less than every 72 hours were not studied in children and adolescents and are not recommended.
  2.3 Administration of Fentanyl Transdermal System
  Fentanyl transdermal system patches are for transdermal use, only.
  Proper handling of fentanyl transdermal system is necessary in order to prevent serious adverse outcomes, including death, associated with accidental secondary exposure to fentanyl transdermal system [see Warnings and Precautions (5.3)].
  Application and Handling Instructions
  - Patients should apply fentanyl transdermal system to intact, non-irritated, and non-irradiated skin on a flat surface such as the chest, back, flank, or upper arm. In young children and persons with cognitive impairment, adhesion should be monitored and the upper back is the preferred location to minimize the potential of inappropriate patch removal. Hair at the application site may be clipped (not shaved) prior to system application. If the site of fentanyl transdermal system application must be cleansed prior to application of the patch, do so with clear water. Do not use soaps, oils, lotions, alcohol, or any other agents that might irritate the skin or alter its characteristics. Allow the skin to dry completely prior to patch application.
  - Patients should apply fentanyl transdermal system immediately upon removal from the sealed package. The patch must not be altered (e.g., cut) in any way prior to application. Fentanyl transdermal system should not be used if the blister seal is broken or if the patch is cut or damaged.
  - The transdermal system is pressed firmly in place with the palm of the hand for 30 seconds, making sure the contact is complete, especially around the edges.
  - Each fentanyl transdermal system patch may be worn continuously for 72 hours. The next patch is applied to a different skin site after removal of the previous transdermal system.
  - If problems with adhesion of the fentanyl transdermal system patch occur, the edges of the patch may be taped with first aid tape. If problems with adhesion persist, the patch may be overlayed with a transparent adhesive film dressing.
  - If the patch falls off before 72 hours, dispose of it by folding in half and flushing down the toilet. A new patch may be applied to a different skin site.
  - Patients (or caregivers who apply fentanyl transdermal system) should wash their hands immediately with soap and water after applying fentanyl transdermal system.
  - Contact with unwashed or unclothed application sites can result in secondary exposure to fentanyl transdermal system and should be avoided. Examples of accidental exposure include transfer of a fentanyl transdermal system patch from an adult’s body to a child while hugging, sharing the same bed as the patient, accidental sitting on a patch and possible accidental exposure of a caregiver’s skin to the medication in the patch while applying or removing the patch.
  - Instruct patients, family members, and caregivers to keep patches in a secure location out of the reach of children and of others for whom fentanyl transdermal system was not prescribed.
  Avoidance of Heat
  Instruct patients to avoid exposing the fentanyl transdermal system application site and surrounding area to direct external heat sources, such as heating pads or electric blankets, heat or tanning lamps, sunbathing, hot baths, saunas, hot tubs, and heated water beds, while wearing the system [see Warnings and Precautions (5.11)].
  2.4 Disposal Instructions
  Failure to properly dispose of fentanyl transdermal system has resulted in accidental exposures and deaths [see Warnings and Precautions (5.3)].
  Patients should dispose of used patches immediately upon removal by folding the adhesive side of the patch to itself, then flushing down the toilet.
  Unused patches should be removed from their pouches, the protective liners removed, the patches folded so that the adhesive side of the patch adheres to itself, and immediately flushed down the toilet.
  Patients should dispose of any patches remaining from a prescription as soon as they are no longer needed.
  2.5 Discontinuation of Fentanyl Transdermal System
  Significant amounts of fentanyl continue to be absorbed from the skin for 24 hours or more after the patch is removed [see Clinical Pharmacology (12.3)].
  To convert patients to another opioid, remove fentanyl transdermal system and titrate the dose of the new analgesic based upon the patient’s report of pain until adequate analgesia has been attained. Upon system removal, 17 hours or more are required for a 50% decrease in serum fentanyl concentrations. Withdrawal symptoms are possible in some patients after conversion or dose adjustment [see Warnings and Precautions (5.17)].
  Do not use Tables 1 and 2 to convert from fentanyl transdermal system to other therapies to avoid overestimating the dose of the new agent resulting in overdose of the new analgesic and possibly death.
  When discontinuing fentanyl transdermal system and not converting to another opioid, use a gradual downward titration, such as halving the dose every 6 days, in order to reduce the possibility of withdrawal symptoms [see Warnings and Precautions (5.17)]. It is not known at what dose level fentanyl transdermal system may be discontinued without producing the signs and symptoms of opioid withdrawal.

DOSAGE FORMS & STRENGTHS SECTION

- Fentanyl transdermal system is available as:
  - Fentanyl Transdermal System 25 mcg/hour (system size 10.7 cm2) is pink in color.
  - Fentanyl Transdermal System 50 mcg/hour (system size 21.4 cm2) is green in color.
  - Fentanyl Transdermal System 75 mcg/hour (system size 32.1 cm2) is blue in color.
  - Fentanyl Transdermal System 100 mcg/hour (system size 42.8 cm2) is gray in color.

CONTRAINDICATIONS SECTION

- Fentanyl transdermal system is contraindicated in the following patients and situations:
  - in patients who are not opioid‑tolerant.
  - in the management of acute or intermittent pain, or in patients who require opioid analgesia for a short period of time.
  - in the management of post-operative pain, including use after out-patient or day surgeries, (e.g., tonsillectomies).
  - in the management of mild pain.
  - in patients with significant respiratory compromise, especially if adequate monitoring and resuscitative equipment are not readily available.
  - in patients who have acute or severe bronchial asthma.
  - in patients who have or are suspected of having paralytic ileus.
  - in patients with known hypersensitivity to fentanyl or any components of the transdermal system. Severe hypersensitivity reactions, including anaphylaxis have been observed with fentanyl transdermal system [see Adverse Reactions (6.2)].

WARNINGS AND PRECAUTIONS SECTION

- 5.1 Addiction, Abuse, and Misuse
  Fentanyl transdermal system contains fentanyl, an opioid agonist and a Schedule II controlled substance. As an opioid, fentanyl transdermal system exposes users to the risks of addiction, abuse, and misuse [see Drug Abuse and Dependence (9)]. As modified-release products such as fentanyl transdermal system deliver the opioid over an extended period of time, there is a greater risk for overdose and death due to the larger amount of fentanyl present.
  Although the risk of addiction in any individual is unknown, it can occur in patients appropriately prescribed fentanyl transdermal system and in those who obtain the drug illicitly. Addiction can occur at recommended doses and if the drug is misused or abused.
  Assess each patient’s risk for opioid addiction, abuse, or misuse prior to prescribing fentanyl transdermal system, and monitor all patients receiving fentanyl transdermal system for the development of these behaviors or conditions. Risks are increased in patients with a personal or family history of substance abuse (including drug or alcohol addiction or abuse) or mental illness (e.g., major depression). The potential for these risks should not, however, prevent the prescribing of fentanyl transdermal system for the proper management of pain in any given patient. Patients at increased risk may be prescribed modified-release opioid formulations such as fentanyl transdermal system, but use in such patients necessitates intensive counseling about the risks and proper use of fentanyl transdermal system along with intensive monitoring for signs of addiction, abuse, and misuse.
  Abuse or misuse of fentanyl transdermal system by placing it in the mouth, chewing it, swallowing it, or using it in ways other than indicated may cause choking, overdose, and death [see Overdosage (10)].
  Opioid agonists such as fentanyl transdermal system are sought by drug abusers and people with addiction disorders and are subject to criminal diversion. Consider these risks when prescribing or dispensing fentanyl transdermal system. Strategies to reduce these risks include prescribing the drug in the smallest appropriate quantity and advising the patient on the proper disposal of unused drug [see Patient Counseling Information (17)]. Contact local state professional licensing board or state controlled substances authority for information on how to prevent and detect abuse or diversion of this product.
  5.2 Life-Threatening Respiratory Depression
  Serious, life-threatening, or fatal respiratory depression has been reported with the use of opioids, even when used as recommended. Respiratory depression from opioid use, if not immediately recognized and treated, may lead to respiratory arrest and death. Management of respiratory depression may include close observation, supportive measures, and use of opioid antagonists, depending on the patient’s clinical status [see Overdosage (10)]. Carbon dioxide (CO2) retention from opioid-induced respiratory depression can exacerbate the sedating effects of opioids.
  Fentanyl transdermal system is indicated only in opioid tolerant patients because of the risk for respiratory depression and death. While serious, life-threatening, or fatal respiratory depression can occur at any time during the use of fentanyl transdermal system, the risk is greatest during the initiation of therapy or following a dose increase. Closely monitor patients for respiratory depression when initiating therapy with fentanyl transdermal system.
  To reduce the risk of respiratory depression, proper dosing and titration of fentanyl transdermal system are essential [see Dosage and Administration (2)]. Overestimating the fentanyl transdermal system dose when converting patients from another opioid product can result in fatal overdose with the first dose.
  Accidental exposure to fentanyl transdermal system, especially in children, can result in respiratory depression and death due to an overdose of fentanyl.
  5.3 Accidental Exposure
  A considerable amount of active fentanyl remains in fentanyl transdermal system even after use as directed. Death and other serious medical problems have occurred when children and adults were accidentally exposed to fentanyl transdermal system. Accidental or deliberate application or ingestion by a child or adolescent will cause respiratory depression that can result in death. Placing fentanyl transdermal system in the mouth, chewing it, swallowing it, or using it in ways other than indicated may cause choking or overdose that could result in death. Improper disposal of fentanyl transdermal system in the trash has resulted in accidental exposures and deaths.
  Advise patients about strict adherence to the recommended handling and disposal instructions in order to prevent accidental exposure to fentanyl transdermal system [see Dosage and Administration (2.4), (2.5)].
  5.4 Neonatal Opioid Withdrawal Syndrome
  Prolonged use of fentanyl transdermal system during pregnancy can result in withdrawal signs in the neonate. Neonatal opioid withdrawal syndrome, unlike opioid withdrawal syndrome in adults, may be life-threatening if not recognized and treated, and requires management according to protocols developed by neonatology experts. If opioid use is required for a prolonged period in a pregnant woman, advise the patient of the risk of neonatal opioid withdrawal syndrome and ensure that appropriate treatment will be available.
  Neonatal opioid withdrawal syndrome presents as irritability, hyperactivity and abnormal sleep pattern, high pitched cry, tremor, vomiting, diarrhea and failure to gain weight. The onset, duration, and severity of neonatal opioid withdrawal syndrome vary based on the specific opioid used, duration of use, timing and amount of last maternal use, and rate of elimination of the drug by the newborn.
  5.5 Interactions with Central Nervous System Depressants
  Hypotension, profound sedation, coma, respiratory depression, and death may result if fentanyl transdermal system is used concomitantly with alcohol or other central nervous system (CNS) depressants (e.g., sedatives, anxiolytics, hypnotics, neuroleptics, other opioids).
  When considering the use of fentanyl transdermal system in a patient taking a CNS depressant, assess the duration use of the CNS depressant and the patient’s response, including the degree of tolerance that has developed to CNS depression. Additionally, evaluate the patient’s use of alcohol or illicit drugs that cause CNS depression. If the decision to begin fentanyl transdermal system is made, reduce the starting dose, monitor patients for signs of sedation and respiratory depression, and consider using a lower dose of the concomitant CNS depressant [see Drug Interactions (7.1)].
  5.6 Use in Elderly, Cachectic, and Debilitated Patients
  Life-threatening respiratory depression is more likely to occur in elderly, cachectic, or debilitated patients as they may have altered pharmacokinetics or altered clearance compared to younger, healthier patients. Monitor such patients closely, particularly when initiating and titrating fentanyl transdermal system and when fentanyl transdermal system is given concomitantly with other drugs that depress respiration [see Warnings and Precautions (5.2)].
  5.7 Chronic Pulmonary Disease
  Monitor patients with significant chronic obstructive pulmonary disease or cor pulmonale, and patients having a substantially decreased respiratory reserve, hypoxia, hypercapnia, or pre-existing respiratory depression for respiratory depression, particularly when initiating therapy with fentanyl transdermal system, as in these patients, even usual therapeutic doses of fentanyl transdermal system may decrease respiratory drive to the point of apnea [see Warnings and Precautions (5.2)]. Consider the use of alternative non-opioid analgesics in these patients if possible.
  5.8 Head Injuries and Increased Intracranial Pressure
  Avoid use of fentanyl transdermal system in patients who may be particularly susceptible to the intracranial effects of CO2 retention such as those with evidence of increased intracranial pressure, impaired consciousness, or coma [see Warnings and Precautions (5.2)]. In addition, opioids may obscure the clinical course of patients with head injury. Monitor patients with brain tumors who may be susceptible to the intracranial effects of CO2 retention for signs of sedation and respiratory depression, particularly when initiating therapy with fentanyl transdermal system, as fentanyl transdermal system may reduce respiratory drive and CO2 retention can further increase intracranial pressure.
  5.9 Hypotensive Effects
  Fentanyl transdermal system may cause severe hypotension including orthostatic hypotension and syncope in ambulatory patients. There is an increased risk in patients whose ability to maintain blood pressure has already been compromised by a reduced blood volume or concurrent administration of certain CNS depressant drugs (e.g., phenothiazines or general anesthetics) [see Drug Interactions (7.1)]. Monitor these patients for signs of hypotension after initiating or titrating the dose of fentanyl transdermal system.
  5.10 Interactions with CYP3A4 Inhibitors and Inducers
  Since the CYP3A4 isoenzyme plays a major role in the metabolism of fentanyl transdermal system, drugs that alter CYP3A4 activity may cause changes in clearance of fentanyl which could lead to changes in fentanyl plasma concentrations.
  The concomitant use of fentanyl transdermal system with a CYP3A4 inhibitors (such as ritonavir, ketoconazole, itraconazole, troleandomycin, clarithromycin, nelfinavir, nefazadone, amiodarone, amprenavir, aprepitant, diltiazem, erythromycin, fluconazole, fosamprenavir, verapamil) may result in an increase in fentanyl plasma concentrations, which could increase or prolong adverse drug effects and may cause potentially fatal respiratory depression. Carefully monitor patients receiving fentanyl transdermal system and any CYP3A4 inhibitor for signs of sedation and respiratory depression for an extended period of time, and make dosage adjustments as needed.
  CYP450 inducers, such as rifampin, carbamazepine, and phenytoin, may induce the metabolism of fentanyl and, therefore, may cause increased clearance of the drug which could lead to a decrease in fentanyl plasma concentrations, lack of efficacy or, possibly, development of an abstinence syndrome in a patient who had developed physical dependence to fentanyl.
  If co-administration is necessary, caution is advised when initiating fentanyl transdermal system treatment in patients currently taking, or discontinuing, CYP3A4 inhibitors or inducers. Evaluate these patients at frequent intervals and consider dose adjustments until stable drug effects are achieved [see Drug Interactions (7.2) and Clinical Pharmacology (12.3)].
  5.11 Application of External Heat
  Exposure to heat may increase fentanyl absorption and there have been reports of overdose and death as a result of exposure to heat. A clinical pharmacology study conducted in healthy adult subjects has shown that the application of heat over the fentanyl transdermal system increased fentanyl exposure [see Clinical Pharmacology (12.3)].
  Warn patients to avoid exposing the fentanyl transdermal system application site and surrounding area to direct external heat sources [see Dosage and Administration (2.3)].
  5.12 Patients with Fever
  Based on a pharmacokinetic model, serum fentanyl concentrations could theoretically increase by approximately one-third for patients with a body temperature of 40°C (104°F) due to temperature-dependent increases in fentanyl released from the system and increased skin permeability. Monitor patients wearing fentanyl transdermal system who develop fever closely for opioid side effects and reduce the fentanyl transdermal system dose if necessary. Warn patients to avoid strenuous exertion that leads to increased core body temperature while wearing fentanyl transdermal system to avoid the risk of potential overdose and death.
  5.13 Cardiac Disease
  Fentanyl transdermal system may produce bradycardia. Monitor patients with bradyarrhythmias closely for changes in heart rate, particularly when initiating therapy with fentanyl transdermal system.
  5.14 Hepatic Impairment
  A clinical pharmacology study with fentanyl transdermal system in patients with cirrhosis has shown that systemic fentanyl exposure increased in these patients. Because of the long half-life of fentanyl when administered as fentanyl transdermal system and hepatic metabolism of fentanyl, avoid use of fentanyl transdermal system in patients with severe hepatic impairment. Insufficient information exists to make precise dosing recommendations regarding the use of fentanyl transdermal system in patients with impaired hepatic function. Therefore, to avoid starting patients with mild to moderate hepatic impairment on too high of a dose, start with one half of the usual dosage of fentanyl transdermal system. Closely monitor for signs of sedation and respiratory depression, including at each dosage increase [see Dosing and Administration (2.2), Use in Specific Populations (8.6) and Clinical Pharmacology (12.3)].
  5.15 Renal Impairment
  A clinical pharmacology study with intravenous fentanyl in patients undergoing kidney transplantation has shown that patients with high blood urea nitrogen level had low fentanyl clearance. Because of the long half-life of fentanyl when administered as fentanyl transdermal system, avoid the use of fentanyl transdermal system in patients with severe renal impairment. Insufficient information exists to make precise dosing recommendations regarding the use of fentanyl transdermal system in patients with impaired renal function. Therefore, to avoid starting patients with mild to moderate renal impairment on too high of a dose, start with one half of the usual dosage of fentanyl transdermal system. Closely monitor for signs of sedation and respiratory depression, including at each dosage increase [see Dosing and Administration (2.2), Use in Specific Populations (8.7) and Clinical Pharmacology (12.3)].
  5.16 Use in Pancreatic/Biliary Tract Disease
  Fentanyl transdermal system may cause spasm of the sphincter of Oddi. Monitor patients with biliary tract disease, including acute pancreatitis for worsened symptoms. Fentanyl transdermal system may cause increases in the serum amylase concentration.
  5.17 Avoidance of Withdrawal
  Avoid the use of mixed agonist/antagonist (i.e., pentazocine, nalbuphine, and butorphanol) or partial agonist (buprenorphine) analgesics in patients who have received or are receiving a course of therapy with an opioid agonist analgesic, including fentanyl transdermal system. In these patients, mixed agonist/antagonist and partial agonist analgesics may reduce the analgesic effect and/or may precipitate withdrawal symptoms.
  5.18 Driving and Operating Machinery
  Strong opioid analgesics impair the mental or physical abilities required for the performance of potentially dangerous tasks, such as driving a car or operating machinery. Warn patients not to drive or operate dangerous machinery unless they are tolerant to the effects of the fentanyl transdermal system.

ADVERSE REACTIONS SECTION

- The following serious adverse reactions are discussed elsewhere in the labeling:
  - Addiction, Abuse, and Misuse [see Warnings and Precautions (5.1)]
  - Life-Threatening Respiratory Depression [see Warnings and Precautions (5.2)]
  - Accidental Exposure [see Warnings and Precautions (5.3)]
  - Neonatal Opioid Withdrawal Syndrome [see Warnings and Precautions (5.4)]
  - Interactions with Central Nervous System Depressants [see Warnings and Precautions (5.5)]
  - Hypotensive Effects [see Warnings and Precautions (5.9)]
  Because clinical trials are conducted under widely varying conditions, adverse reaction rates observed in the clinical trials of a drug cannot be directly compared to rates in the clinical trials of another drug and may not reflect the rates observed in clinical practice.
  6.1 Clinical Trial Experience
  The safety of fentanyl transdermal system was evaluated in 216 patients who took at least one dose of fentanyl transdermal system in a multicenter, double-blind, randomized, placebo-controlled clinical trial of fentanyl transdermal system. This trial examined patients over 40 years of age with severe pain induced by osteoarthritis of the hip or knee and who were in need of and waiting for joint replacement.
  The most common adverse reactions (≥5%) in a double-blind, randomized, placebo-controlled clinical trial in patients with severe pain were nausea, vomiting, somnolence, dizziness, insomnia, constipation, hyperhidrosis, fatigue, feeling cold, and anorexia. Other common adverse reactions (≥5%) reported in clinical trials in patients with chronic malignant or nonmalignant pain were headache and diarrhea. Adverse reactions reported for ≥1% of fentanyl transdermal system-treated patients and with an incidence greater than placebo-treated patients are shown in Table 3.
  The most common adverse reactions that were associated with discontinuation in patients with pain (causing discontinuation in ≥1% of patients) were depression, dizziness, somnolence, headache, nausea, vomiting, constipation, hyperhidrosis, and fatigue.
  Table 3. Adverse Reactions Reported by ≥1% of Fentanyl Transdermal System-treated Patients and With an Incidence Greater Than Placebo-treated Patients in 1 Double-Blind, Placebo-Controlled Clinical Trial of Fentanyl Transdermal System
  System/Organ Class Adverse Reaction | Fentanyl Transdermal System %(N=216) | Placebo%(N=200)
  Cardiac disorders
  Palpitations | 4 | 1
  Ear and labyrinth disorders
  Vertigo | 2 | 1
  Gastrointestinal disorders
  Nausea | 41 | 17
  Vomiting | 26 | 3
  Constipation | 9 | 1
  Abdominal pain upper | 3 | 2
  Dry mouth | 2 | 0
  General disorders and administration site conditions
  Fatigue | 6 | 3
  Feeling cold | 6 | 2
  Malaise | 4 | 1
  Asthenia | 2 | 0
  Edema peripheral | 1 | 1
  Metabolism and nutrition disorders
  Anorexia | 5 | 0
  Musculoskeletal and connective tissue disorders
  Muscle spasms | 4 | 2
  Nervous system disorders
  Somnolence | 19 | 3
  Dizziness | 10 | 4
  Psychiatric disorders
  Insomnia | 10 | 7
  Depression | 1 | 0
  Skin and subcutaneous tissue disorders
  Hyperhidrosis | 6 | 1
  Pruritus | 3 | 2
  Rash | 2 | 1
  Adverse reactions not reported in Table 1 that were reported by ≥1% of fentanyl transdermal system‑treated adult and pediatric patients (N=1854) in 11 controlled and uncontrolled clinical trials of fentanyl transdermal system used for the treatment of chronic malignant or nonmalignant pain are shown in Table 4.
  Table 4. Adverse Reactions Reported by ≥1% of Fentanyl Transdermal System-treated Patients in 11 Clinical Trials of Fentanyl Transdermal System
  System/Organ Class Adverse Reaction | Fentanyl Transdermal System%(N=1854)
  Gastrointestinal disorders
  Diarrhea | 10
  Abdominal pain | 3
  Immune system disorders
  Hypersensitivity | 1
  Nervous system disorders
  Headache | 12
  Tremor | 3
  Paresthesia | 2
  Psychiatric disorders
  Anxiety | 3
  Confusional state | 2
  Hallucination | 1
  Renal and urinary disorders
  Urinary retention | 1
  Skin and subcutaneous tissue disorders
  Erythema | 1
  The following adverse reactions occurred in adult and pediatric patients with an overall frequency of <1% and are listed in descending frequency within each System/Organ Class:
  Cardiac disorders: cyanosis
  Eye disorders: miosis
  Gastrointestinal disorders: subileus
  General disorders and administration site conditions: application site reaction, influenza-like illness, application site hypersensitivity, drug withdrawal syndrome, application site dermatitis
  Musculoskeletal and connective tissue disorders: muscle twitching
  Nervous system disorders: hypoesthesia
  Psychiatric disorders: disorientation, euphoric mood
  Reproductive system and breast disorders: erectile dysfunction, sexual dysfunction
  Respiratory, thoracic and mediastinal disorders: respiratory depression
  Skin and subcutaneous tissue disorders: eczema, dermatitis allergic, dermatitis contact
  Pediatrics
  The safety of fentanyl transdermal system was evaluated in three open-label trials in 289 pediatric patients with chronic pain, 2 years of age through 18 years of age. Adverse reactions reported by ≥1% of fentanyl transdermal system-treated pediatric patients are shown in Table 5.
  Table 5. Adverse Reactions Reported by ≥1% of Fentanyl Transdermal System-treated Pediatric Patients in 3 Clinical Trials of Fentanyl Transdermal System
  System/Organ Class Adverse Reaction | Fentanyl Transdermal System%(N=289)
  Gastrointestinal disorders
  Vomiting | 34
  Nausea | 24
  Constipation | 13
  Diarrhea | 13
  Abdominal pain | 9
  Abdominal pain upper | 4
  Dry mouth | 2
  General disorders and administration site conditions
  Edema peripheral | 5
  Fatigue | 2
  Application site reaction | 1
  Asthenia | 1
  Immune system disorders
  Hypersensitivity | 3
  Metabolism and nutrition disorders
  Anorexia | 4
  Musculoskeletal and connective tissue disorders
  Muscle spasms | 2
  Nervous system disorders
  Headache | 16
  Somnolence | 5
  Dizziness | 2
  Tremor | 2
  Hypoesthesia | 1
  Psychiatric disorders
  Insomnia | 6
  Anxiety | 4
  Depression | 2
  Hallucination | 2
  Renal and urinary disorders
  Urinary retention | 3
  Respiratory, thoracic and mediastinal disorders
  Respiratory depression | 1
  Skin and subcutaneous tissue disorders
  Pruritus | 13
  Rash | 6
  Hyperhidrosis | 3
  Erythema | 3
  6.2 Post-Marketing Experience
  The following adverse reactions have been identified during post-approval use of fentanyl transdermal system. Because these reactions are reported voluntarily from a population of uncertain size, it is not always possible to reliably estimate their frequency.
  Cardiac Disorders: tachycardia, bradycardia
  Eye Disorders: vision blurred
  Gastrointestinal Disorders: ileus, dyspepsia
  General disorders and administration site conditions: pyrexia
  Immune system disorders: anaphylactic shock, anaphylactic reaction, anaphylactoid reaction
  Investigations: weight decreased
  Nervous System Disorders: convulsions (including clonic convulsions and grand mal convulsion), amnesia, depressed level of consciousness, loss of consciousness
  Psychiatric Disorders: agitation
  Respiratory, Thoracic, and Mediastinal Disorders: respiratory distress, apnea, bradypnea, hypoventilation, dyspnea
  Vascular Disorders: hypotension, hypertension

DRUG INTERACTIONS SECTION

- 7.1 Central Nervous System Depressants
  The concomitant use of fentanyl transdermal system with other CNS depressants, including sedatives, hypnotics, tranquilizers, general anesthetics, phenothiazines, other opioids, and alcohol, can increase the risk of respiratory depression, profound sedation, coma and death. Monitor patients receiving CNS depressants and fentanyl transdermal system for signs of respiratory depression, sedation and hypotension.
  When combined therapy with any of the above medications is considered, the dose of one or both agents should be reduced [see Dosage and Administration (2.2) and Warnings and Precautions (5.5)].
  7.2 Drugs Affecting Cytochrome P450 3A4 Isoenzymes
  Inhibitors of CYP3A4
  Because the CYP3A4 isoenzyme plays a major role in the metabolism of fentanyl, drugs that inhibit CYP3A4 activity may cause decreased clearance of fentanyl which could lead to an increase in fentanyl plasma concentrations and result in increased or prolonged opioid effects. These effects could be more pronounced with concomitant use of 3A4 inhibitors. If co-administration with fentanyl transdermal system is necessary, monitor patients for respiratory depression and sedation at frequent intervals and consider dose adjustments until stable drug effects are achieved [see Clinical Pharmacology (12.3)].
  Inducers of CYP3A4
  CYP450 3A4 inducers may induce the metabolism of fentanyl and, therefore, may cause increased clearance of the drug which could lead to a decrease in fentanyl plasma concentrations, lack of efficacy or, possibly, development of a withdrawal syndrome in a patient who had developed physical dependence to fentanyl. If co-administration with fentanyl transdermal system is necessary, monitor for signs of opioid withdrawal and consider dose adjustments until stable drug effects are achieved [see Clinical Pharmacology (12.3)].
  After stopping the treatment of a CYP3A4 inducer, as the effects of the inducer decline, the fentanyl plasma concentration will increase which could increase or prolong both the therapeutic and adverse effects, and may cause serious respiratory depression [see Clinical Pharmacology (12.3)].
  7.3 MAO Inhibitors
  Avoid use of fentanyl transdermal system in the patient who would require the concomitant administration of a monoamine oxidase (MAO) inhibitor, or within 14 days of stopping such treatment because severe and unpredictable potentiation by MAO inhibitors has been reported with opioid analgesics.
  7.4 Mixed Agonist/Antagonist and Partial Agonist Opioid Analgesics
  Mixed agonist/antagonist (i.e., pentazocine, nalbuphine, and butorphanol) and partial agonist (buprenorphine) analgesics may reduce the analgesic effect of fentanyl transdermal system or may precipitate withdrawal symptoms. Avoid the use of agonist/antagonist and partial agonist analgesics in patients receiving fentanyl transdermal system.
  7.5 Anticholinergics
  Anticholinergics or other medications with anticholinergic activity when used concurrently with opioid analgesics may result in increased risk of urinary retention and/or severe constipation, which may lead to paralytic ileus. Monitor patients for signs of urinary retention or reduced gastrointestinal motility when fentanyl transdermal system is used concurrently with anticholinergic drugs.

USE IN SPECIFIC POPULATIONS SECTION

- 8.1 Pregnancy
  Clinical Considerations
  Fetal/neonatal adverse reactions
  Prolonged use of opioid analgesics during pregnancy for medical or nonmedical purposes can result in physical dependence in the neonate and neonatal opioid withdrawal syndrome shortly after birth. Observe newborns for symptoms of neonatal opioid withdrawal syndrome, such as poor feeding, diarrhea, irritability, tremor, rigidity, and seizures, and manage accordingly [see Warnings and Precautions (5.4)].
  Teratogenic Effects
  Pregnancy C: There are no adequate and well-controlled studies in pregnant women. Fentanyl transdermal system should be used during pregnancy only if the potential benefit justifies the potential risk to the fetus.
  The potential effects of fentanyl on embryo-fetal development were studied in the rat, mouse, and rabbit models. Published literature reports that administration of fentanyl (0, 10, 100, or 500 mcg/kg/day) to pregnant female Sprague-Dawley rats from day 7 to 21 via implanted microosmotic minipumps did not produce any evidence of teratogenicity (the high dose is approximately 2 times the daily human dose administered by a 100 mcg/hr patch on a mg/m2 basis). In contrast, the intravenous administration of fentanyl (0, 0.01, or 0.03 mg/kg) to bred female rats from gestation day 6 to 18 suggested evidence of embryo-toxicity and a slight increase in mean delivery time in the 0.03 mg/kg/day group. There was no clear evidence of teratogenicity noted.
  Pregnant female New Zealand White rabbits were treated with fentanyl (0, 0.025, 0.1, 0.4 mg/kg) via intravenous infusion from day 6 to day 18 of pregnancy. Fentanyl produced a slight decrease in the body weight of the live fetuses at the high dose, which may be attributed to maternal toxicity. Under the conditions of the assay, there was no evidence for fentanyl induced adverse effects on embryo-fetal development at doses up to 0.4 mg/kg (approximately 3 times the daily human dose administered by a 100 mcg/h patch on a mg/m2 basis).
  Nonteratogenic Effects
  Chronic maternal treatment with fentanyl during pregnancy has been associated with transient respiratory depression, behavioral changes, or seizures characteristic of neonatal abstinence syndrome in newborn infants. Symptoms of neonatal respiratory or neurological depression were no more frequent than expected in most studies of infants born to women treated acutely during labor with intravenous or epidural fentanyl. Transient neonatal muscular rigidity has been observed in infants whose mothers were treated with intravenous fentanyl.
  The potential effects of fentanyl on prenatal and postnatal development were examined in the rat model. Female Wistar rats were treated with 0, 0.025, 0.1, or 0.4 mg/kg/day fentanyl via intravenous infusion from day 6 of pregnancy through 3 weeks of lactation. Fentanyl treatment (0.4 mg/kg/day) significantly decreased body weight in male and female pups and also decreased survival in pups at day 4. Both the mid-dose and high-dose of fentanyl animals demonstrated alterations in some physical landmarks of development (delayed incisor eruption and eye opening) and transient behavioral development (decreased locomotor activity at day 28 which recovered by day 50). The mid-dose and the high-dose are 0.4 and 1.6 times the daily human dose administered by a 100 mcg/hr patch on a mg/m2 basis.
  8.2 Labor and Delivery
  Opioids cross the placenta and may produce respiratory depression in neonates. Fentanyl transdermal system is not for use in women during and immediately prior to labor, when shorter acting analgesics or other analgesic techniques are more appropriate. Opioid analgesics can prolong labor through actions that temporarily reduce the strength, duration, and frequency of uterine contractions. However, this effect is not consistent and may be offset by an increased rate of cervical dilatation, which tends to shorten labor.
  8.3 Nursing Mothers
  Fentanyl is excreted in human milk; therefore, fentanyl transdermal system is not recommended for use in nursing women because of the possibility of effects in their infants.
  8.4 Pediatric Use
  The safety of fentanyl transdermal system was evaluated in three open-label trials in 289 pediatric patients with chronic pain, 2 years of age through 18 years of age. Starting doses of 25 mcg/h and higher were used by 181 patients who had been on prior daily opioid doses of at least 45 mg/day of oral morphine or an equianalgesic dose of another opioid. Initiation of fentanyl transdermal system therapy in pediatric patients taking less than 60 mg/day of oral morphine or an equianalgesic dose of another opioid has not been evaluated in controlled clinical trials.
  The safety and effectiveness of fentanyl transdermal system in children under 2 years of age have not been established.
  To guard against excessive exposure to fentanyl transdermal system by young children, advise caregivers to strictly adhere to recommended fentanyl transdermal system application and disposal instructions [see Dosage and Administration (2.4), (2.5) and Warnings and Precautions (5.3)].
  8.5 Geriatric Use
  Clinical studies of fentanyl transdermal system did not include sufficient numbers of subjects aged 65 and over to determine whether they respond differently from younger subjects. Other reported clinical experience has not identified differences in responses between the elderly and younger patients. In general, dose selection for an elderly patient should be cautious, usually starting at the low end of the dosing range, reflecting the greater frequency of decreased hepatic, renal, or cardiac function, and of concomitant disease or other drug therapy.
  Data from intravenous studies with fentanyl suggest that the elderly patients may have reduced clearance and a prolonged half-life. Moreover, elderly patients may be more sensitive to the active substance than younger patients. A study conducted with the fentanyl transdermal system patch in elderly patients demonstrated that fentanyl pharmacokinetics did not differ significantly from young adult subjects, although peak serum concentrations tended to be lower and mean half-life values were prolonged to approximately 34 hours [see Clinical Pharmacology (12.3)].
  Monitor geriatric patients closely for signs of sedation and respiratory depression, particularly when initiating therapy with fentanyl transdermal system and when given in conjunction with other drugs that depress respiration [see Warnings and Precautions (5.2), (5.6)].
  8.6 Hepatic Impairment
  The effect of hepatic impairment on the pharmacokinetics of fentanyl transdermal system has not been fully evaluated. A clinical pharmacology study with fentanyl transdermal system in patients with cirrhosis has shown that systemic fentanyl exposure increased in these patients. Because there is in-vitro and in-vivo evidence of extensive hepatic contribution to the elimination of fentanyl transdermal system, hepatic impairment would be expected to have significant effects on the pharmacokinetics of fentanyl transdermal system. Avoid use of fentanyl transdermal system in patients with severe hepatic impairment [see Dosing and Administration (2.1), Warnings and Precautions (5.14) and Clinical Pharmacology 12.3)].
  8.7 Renal Impairment
  The effect of renal impairment on the pharmacokinetics of fentanyl transdermal system has not been fully evaluated. A clinical pharmacology study with intravenous fentanyl in patients undergoing kidney transplantation has shown that patients with high blood urea nitrogen level had low fentanyl clearance. Because there is in-vivo evidence of renal contribution to the elimination of fentanyl transdermal system, renal impairment would be expected to have significant effects on the pharmacokinetics of fentanyl transdermal system. Avoid the use of fentanyl transdermal system in patients with severe renal impairment [see Dosing and Administration (2.1), Warnings and Precautions (5.15) and Clinical Pharmacology (12.3)].

DRUG ABUSE AND DEPENDENCE SECTION

- 9.1 Controlled Substance
  Fentanyl transdermal system contains fentanyl, a Schedule II controlled substance with a high potential for abuse similar to other opioids including morphine, hydromorphone, methadone, oxycodone, and oxymorphone. Fentanyl transdermal system can be abused and is subject to misuse, addiction, and criminal diversion [see Warnings and Precautions (5.1)].
  The high drug content in extended-release formulations adds to the risk of adverse outcomes from abuse and misuse.
  9.2 Abuse
  All patients treated with opioids require careful monitoring for signs of abuse and addiction, since use of opioid analgesic products carries the risk of addiction even under appropriate medical use.
  Drug abuse is the intentional non-therapeutic use of an over-the-counter or prescription drug, even once, for its rewarding psychological or physiological effects. Drug abuse includes, but is not limited to, the following examples: the use of a prescription or over-the-counter drug to get "high", or the use of steroids for performance enhancement and muscle build up.
  Drug addiction is a cluster of behavioral, cognitive, and physiological phenomena that develop after repeated substance use and include: a strong desire to take the drug, difficulties in controlling its use, persisting in its use despite harmful consequences, a higher priority given to drug use than to other activities and obligations, increased tolerance, and sometimes a physical withdrawal.
  "Drug seeking" behavior is very common in addicts and drug abusers. Drug-seeking tactics include emergency calls or visits near the end of office hours, refusal to undergo appropriate examination, testing or referral, repeated "loss" of prescriptions, tampering with prescriptions and reluctance to provide prior medical records or contact information for other treating physician(s). "Doctor shopping" to obtain additional prescriptions is common among drug abusers and people suffering from untreated addiction. Preoccupation with achieving pain relief can be appropriate behavior in a patient with poor pain control.
  Abuse and addiction are separate and distinct from physical dependence and tolerance. Physicians should be aware that addiction may be accompanied by concurrent tolerance and symptoms of physical dependence in all addicts. Fentanyl transdermal system, like other opioids, can be diverted for non-medical use into illicit channels of distribution. Careful recordkeeping of prescribing information, including quantity, frequency, and renewal requests, as required by state law, is strongly advised.
  Proper assessment of the patient, proper prescribing practices, periodic reevaluation of therapy, and proper dispensing and storage are appropriate measures that help to limit abuse of opioid drugs.
  Risks Specific to the Abuse of Fentanyl transdermal system
  Fentanyl transdermal system is intended for transdermal use only. Abuse of fentanyl transdermal system poses a risk of overdose and death. This risk is increased with concurrent abuse of fentanyl transdermal system with alcohol and other central nervous system depressants [see Warnings and Precautions (5.5), and Drug Interactions (7.1)]. Intentional compromise of the transdermal delivery system may result in the uncontrolled delivery of fentanyl and pose a significant risk to the abuser that could result in overdose and death [see Warnings and Precautions (5.1)]. Abuse may occur by applying the transdermal system in the absence of legitimate purpose, or by swallowing, snorting or injecting fentanyl extracted from the transdermal system.
  9.3 Dependence
  Both tolerance and physical dependence can develop during chronic opioid therapy. Tolerance is the need for increasing doses of opioids to maintain a defined effect such as analgesia (in the absence of disease progression or other external factors). Tolerance may occur to both the desired and undesired effects of drugs, and may develop at different rates for different effects.
  Physical dependence results in withdrawal symptoms after abrupt discontinuation or a significant dose reduction of a drug. Withdrawal also may be precipitated through the administration of drugs with opioid antagonist activity, e.g., naloxone, nalmefene, mixed agonist/antagonist analgesics (pentazocine, butorphanol, nalbuphine), or partial agonists (buprenorphine). Physical dependence may not occur to a clinically significant degree until after several days to weeks of continued opioid usage.
  Fentanyl transdermal system should not be abruptly discontinued [see Dosage and Administration (2.5)]. If fentanyl transdermal system is abruptly discontinued in a physically-dependent patient, an abstinence syndrome may occur. Some or all of the following can characterize this syndrome: restlessness, lacrimation, rhinorrhea, yawning, perspiration, chills, myalgia, and mydriasis. Other signs and symptoms also may develop, including: irritability, anxiety, backache, joint pain, weakness, abdominal cramps, insomnia, nausea, anorexia, vomiting, diarrhea, or increased blood pressure, respiratory rate, or heart rate.
  Infants born to mothers physically dependent on opioids will also be physically dependent and may exhibit respiratory difficulties and withdrawal symptoms [see Use in Specific Populations (8.2, 8.3)].

OVERDOSAGE SECTION

- 10.1 Clinical Presentation
  Acute overdosage with opioids can be manifested by respiratory depression, somnolence progressing to stupor or coma, skeletal muscle flaccidity, cold and clammy skin, constricted pupils, and sometimes bradycardia, hypotension and death. The pharmacokinetic characteristics of fentanyl transdermal system must also be taken into account when treating the overdose. Even in the face of improvement, continued medical monitoring is required because of the possibility of extended effects. Deaths due to overdose have been reported with abuse and misuse of fentanyl transdermal system.
  10.2 Treatment of Overdose
  Give primary attention to the reestablishment of a patent airway and institution of assisted or controlled ventilation. Employ supportive measures (including oxygen and vasopressors) in the management of circulatory shock and pulmonary edema accompanying overdose as indicated. Cardiac arrest or arrhythmias will require advanced life support techniques. Remove all fentanyl transdermal systems.
  The pure opioid antagonists, such as naloxone, are specific antidotes to respiratory depression from opioid overdose. Since the duration of reversal is expected to be less than the duration of action of fentanyl, carefully monitor the patient until spontaneous respiration is reliably reestablished. After fentanyl transdermal system removal, serum fentanyl concentrations decline gradually, falling about 50% in approximately 20 to 27 hours. Therefore, management of an overdose must be monitored accordingly, at least 72 to 96 hours beyond the overdose.
  Only administer opioid antagonists in the presence of clinically significant respiratory or circulatory depression secondary to hydromorphone overdose. In patients who are physically dependent on any opioid agonist including fentanyl transdermal system, an abrupt or complete reversal of opioid effects may precipitate an acute abstinence syndrome. The severity of the withdrawal syndrome produced will depend on the degree of physical dependence and the dose of the antagonist administered. Please see the prescribing information for the specific opioid antagonist for details of their proper use.

DESCRIPTION SECTION

- Fentanyl transdermal system is a transdermal system containing fentanyl. The chemical name is N‑phenyl-N-(1-(2-phenylethyl)-4-piperidinyl) propanamide. The structural formula is:
  The molecular weight of fentanyl base is 336.5, and the empirical formula is C22H28N2O. The n‑octanol: water partition coefficient is 860:1. The pKa is 8.4.
  System Components and Structure
  The amount of fentanyl released from each system per hour is proportional to the surface area (25 mcg/h per 10.7 cm2). The composition per unit area of all system sizes is identical.
  Dose* (mcg/h) | Size (cm2) | Fentanyl Content (mg) | Color of Printing on Back of Patch
  25 | 10.7 | 2.76 | Pink
  50 | 21.4 | 5.52 | Green
  75 | 32.1 | 8.28 | Blue
  100 | 42.8 | 11.04 | Gray
  *Nominal delivery rate per hour
  Fentanyl transdermal system is a rectangular transparent unit comprising a protective liner and two functional layers. Proceeding from the outer surface toward the surface adhering to skin, these layers are:
  1) a backing layer of polyethylene/aluminum/polyester film; 2) a drug-in-adhesive layer. Before use, a protective liner covering the adhesive layer is removed and discarded.

CLINICAL PHARMACOLOGY SECTION

- 12.1 Mechanism of Action
  Fentanyl is an opioid analgesic. Fentanyl interacts predominately with the opioid mu‑receptor. These mu-binding sites are distributed in the human brain, spinal cord, and other tissues.
  12.2 Pharmacodynamics
  Central Nervous System Effects
  Fentanyl exerts its principal pharmacologic effects on the central nervous system. Central nervous system effects increase with increasing serum fentanyl concentrations.
  In addition to analgesia, alterations in mood, euphoria, dysphoria, and drowsiness commonly occur. Fentanyl depresses the respiratory centers, depresses the cough reflex, and constricts the pupils. Analgesic blood concentrations of fentanyl may cause nausea and vomiting directly by stimulating the chemoreceptor trigger zone, but nausea and vomiting are significantly more common in ambulatory than in recumbent patients, as is postural syncope.
  Ventilatory Effects
  In clinical trials of 357 non-opioid tolerant subjects treated with fentanyl transdermal system, 13 subjects experienced hypoventilation. Hypoventilation was manifested by respiratory rates of less than 8 breaths/minute or a pCO2 greater than 55 mm Hg. In these studies, the incidence of hypoventilation was higher in nontolerant women (10) than in men (3) and in subjects weighing less than 63 kg (9 of 13). Although subjects with prior impaired respiration were not common in the trials, they had higher rates of hypoventilation. In addition, post-marketing reports have been received that describe opioid-naive post-operative patients who have experienced clinically significant hypoventilation and death with fentanyl transdermal system.
  Hypoventilation can occur throughout the therapeutic range of fentanyl serum concentrations, especially for patients who have an underlying pulmonary condition or who receive concomitant opioids or other CNS drugs associated with hypoventilation. The use of fentanyl transdermal system is contraindicated in patients who are not tolerant to opioid therapy.
  Gastrointestinal Tract and Other Smooth Muscle
  Opioids increase the tone and decrease the propulsive contractions of the smooth muscle of the gastrointestinal tract. The resultant prolongation in gastrointestinal transit time may be responsible for the constipating effect of fentanyl. Because opioids may increase biliary tract pressure, some patients with biliary colic may experience worsening rather than relief of pain.
  While opioids generally increase the tone of urinary tract smooth muscle, the net effect tends to be variable, in some cases producing urinary urgency, in others, difficulty in urination.
  Cardiovascular Effects
  Fentanyl may cause orthostatic hypotension and fainting. Fentanyl may infrequently produce bradycardia. The incidence of bradycardia in clinical trials with fentanyl transdermal system was less than 1%.
  Histamine assays and skin wheal testing in clinical studies indicate that clinically significant histamine release rarely occurs with fentanyl administration. Clinical assays show no clinically significant histamine release in dosages up to 50 mcg/kg.
  12.3 Pharmacokinetics
  Absorption
  Fentanyl transdermal system is a drug-in-adhesive matrix designed formulation. Fentanyl is released from the matrix at a nearly constant amount per unit time. The concentration gradient existing between the matrix and the lower concentration in the skin drives drug release. Fentanyl moves in the direction of the lower concentration at a rate determined by the matrix and the diffusion of fentanyl through the skin layers. While the actual rate of fentanyl delivery to the skin varies over the 72-hour application period, each system is labeled with a nominal flux which represents the average amount of drug delivered to the systemic circulation per hour across average skin.
  While there is variation in dose delivered among patients, the nominal flux of the systems (25, 50, 75, and 100 mcg of fentanyl per hour) is sufficiently accurate as to allow individual titration of dosage for a given patient.
  Following fentanyl transdermal system application, the skin under the system absorbs fentanyl, and a depot of fentanyl concentrates in the upper skin layers. Fentanyl then becomes available to the systemic circulation. Serum fentanyl concentrations increase gradually following initial fentanyl transdermal system application, generally leveling off between 12 and 24 hours and remaining relatively constant, with some fluctuation, for the remainder of the 72-hour application period. Peak serum concentrations of fentanyl generally occurred between 20 and 72 hours after initial application (see Table 6). Serum fentanyl concentrations achieved are proportional to the fentanyl transdermal system delivery rate. With continuous use, serum fentanyl concentrations continue to rise for the first two system applications. By the end of the second 72-hour application, a steady-state serum concentration is reached and is maintained during subsequent applications of a patch of the same size (see Figure 1). Patients reach and maintain a steady-state serum concentration that is determined by individual variation in skin permeability and body clearance of fentanyl.
  After system removal, serum fentanyl concentrations decline gradually, falling about 50% in approximately 20 to 27 hours. Continued absorption of fentanyl from the skin accounts for a slower disappearance of the drug from the serum than is seen after an IV infusion, where the apparent half-life is approximately 7 (range 3 to 12) hours.
  A clinical pharmacology study conducted in healthy adult subjects has shown that the application of heat over the fentanyl transdermal system increased mean overall fentanyl exposure by 120% and average maximum fentanyl level by 61%.
  Table 6: FENTANYL PHARMACOKINETIC PARAMETERS FOLLOWING FIRST 72-HOUR APPLICATION OF FENTANYL TRANSDERMAL SYSTEM
   | Mean (SD) Time to Maximal Concentration Tmax (h) | Mean (SD) Maximal Concentration Cmax (ng/mL)
  Fentanyl Transdermal System 25 mcg/h | 31.7 (16.5) | 0.85 (0.26)**
  Fentanyl Transdermal System 50 mcg/h | 32.8 (15.6) | 1.72 (0.53)**
  Fentanyl Transdermal System 75 mcg/h | 35.8 (14.1) | 2.32 (0.86)**
  Fentanyl Transdermal System 100 mcg/h | 29.9 (13.3) | 3.36 (1.28)**
  ** Cmax values: Study C-2002-048 dose proportionality study in healthy volunteers
  NOTE: After system removal there is continued systemic absorption from residual fentanyl in the skin so that serum concentrations fall 50%, on average, in approximately 20 to 27 hours.
  Figure 1 Serum Fentanyl Concentrations
  Following Single and Multiple Applications of Fentanyl Transdermal System 100 mcg/h
  Table 7: RANGE OF PHARMACOKINETIC PARAMETERS OF INTRAVENOUS FENTANYL IN PATIENTS
   | Clearance (L/h) Range[70 kg] | Volume of Distribution VSS (L/kg) Range | Half-Life t1/2 (h) Range
  Surgical Patients | 27 - 75 | 3 - 8 | 3 - 12
  Hepatically Impaired Patients | 3 - 80+ | 0.8 - 8+ | 4 - 12+
  Renally Impaired Patients | 30 - 78 | – | –
  +Estimated
  NOTE: Information on volume of distribution and half-life not available for renally impaired patients.
  Distribution
  Fentanyl plasma protein binding capacity decreases with increasing ionization of the drug. Alterations in pH may affect its distribution between plasma and the central nervous system. Fentanyl accumulates in the skeletal muscle and fat and is released slowly into the blood. The average volume of distribution for fentanyl is 6 L/kg (range 3 to 8; N=8).
  Metabolism
  Fentanyl is metabolized primarily via human cytochrome P450 3A4 isoenzyme system. In humans, the drug appears to be metabolized primarily by oxidative N‑dealkylation to norfentanyl and other inactive metabolites that do not contribute materially to the observed activity of the drug.
  Excretion
  Within 72 hours of IV fentanyl administration, approximately 75% of the dose is excreted in urine, mostly as metabolites with less than 10% representing unchanged drug. Approximately 9% of the dose is recovered in the feces, primarily as metabolites. Mean values for unbound fractions of fentanyl in plasma are estimated to be between 13 and 21%.
  Skin does not appear to metabolize fentanyl delivered transdermally. This was determined in a human keratinocyte cell assay and in clinical studies in which 92% of the dose delivered from the system was accounted for as unchanged fentanyl that appeared in the systemic circulation.
  Specific Populations
  Geriatric Use
  Data from intravenous studies with fentanyl suggest that the elderly patients may have reduced clearance and a prolonged half-life. Moreover elderly patients may be more sensitive to the active substance than younger patients. A study conducted with the fentanyl transdermal patch in elderly patients demonstrated that fentanyl pharmacokinetics did not differ significantly from young adult subjects, although peak serum concentrations tended to be lower and mean half-life values were prolonged to approximately 34 hours. In this study, a single fentanyl transdermal system 100 mcg/hour patch was applied to a skin site on the upper outer arm in a group of healthy elderly Caucasians ≥65 years old (n=21, mean age 71 years) and worn for 72 hours. The mean Cmax and AUC∞ values were approximately 8% lower and 7% higher, respectively, in the elderly subjects as compared with subjects 18 to 45 years old. Inter-subject variability in AUC∞ was higher in elderly subjects than in healthy adult subjects 18 to 45 years (58% and 37%, respectively). The mean half-life value was longer in subjects ≥65 years old than in subjects 18 to 45 years old (34.4 hours versus 23.5 hours) [see Warnings and Precautions (5.6) and Use in Specific Populations (8.5)].
  Pediatric Use
  In 1.5 to 5 year old, non-opioid-tolerant pediatric patients, the fentanyl plasma concentrations were approximately twice as high as that of adult patients. In older pediatric patients, the pharmacokinetic parameters were similar to that of adults. However, these findings have been taken into consideration in determining the dosing recommendations for opioid-tolerant pediatric patients (2 years of age and older). For pediatric dosing information, refer to [see Dosing and Administration (2.1)].
  Hepatic Impairment
  Information on the effect of hepatic impairment on the pharmacokinetics of fentanyl transdermal system is limited. The pharmacokinetics of fentanyl transdermal system delivering 50 mcg/hour of fentanyl for 72 hours was evaluated in patients hospitalized for surgery. Compared to the controlled patients (n=8), Cmax and AUC in the patients with cirrhosis (n=9) increased 35% and 73%, respectively.
  Because there is in-vitro and in-vivo evidence of extensive hepatic contribution to the elimination of fentanyl transdermal system, hepatic impairment would be expected to have significant effects on the pharmacokinetics of fentanyl transdermal system. Avoid use of fentanyl transdermal system in patients with severe hepatic impairment [see Dosing and Administration (2.1), Warnings and Precautions (5.14), and Use in Specific Populations (8.6)].
  Renal Impairment
  Information on the effect of renal impairment on the pharmacokinetics of fentanyl transdermal system is limited. The pharmacokinetics of intravenous injection of 25 mcg/kg fentanyl was evaluated in patients (n=8) undergoing kidney transplantation. An inverse relationship between blood urea nitrogen level and fentanyl clearance was found.
  Because there is in-vivo evidence of renal contribution to the elimination of fentanyl transdermal system, renal impairment would be expected to have significant effects on the pharmacokinetics of fentanyl transdermal system. Avoid the use of fentanyl transdermal system in patients with severe renal impairment [see Dosing and Administration (2.1), Warnings and Precautions (5.15) and Use in Specific Populations (8.7)].
  Drug-Drug Interactions
  CYP3A4 Inhibitors
  Fentanyl is metabolized mainly via the human cytochrome P450 3A4 isoenzyme system (CYP3A4). The interaction between ritonavir, a CYP3A4 inhibitor, and fentanyl was investigated in eleven healthy volunteers in a randomized crossover study. Subjects received oral ritonavir or placebo for 3 days. The ritonavir dose was 200 mg tid. on Day 1 and 300 mg tid. on Day 2 followed by one morning dose of 300 mg on Day 3. On Day 2, fentanyl was given as a single IV dose at 5 mcg/kg two hours after the afternoon dose of oral ritonavir or placebo. Naloxone was administered to counteract the side effects of fentanyl. The results suggested that ritonavir might decrease the clearance of fentanyl by 67%, resulting in a 174% (range 52% -420%) increase in fentanyl AUC0-∞. The concomitant use of transdermal fentanyl with all CYP3A4 inhibitors (such as ritonavir, ketoconazole, itraconazole, troleandomycin, clarithromycin, nelfinavir, nefazadone, amiodarone, amprenavir, aprepitant, diltiazem, erythromycin, fluconazole, fosamprenavir, verapamil, or grapefruit juice) may result in an increase in fentanyl plasma concentrations, which could increase or prolong adverse drug effects and may cause potentially fatal respiratory depression. Carefully monitor patients receiving fentanyl transdermal system and any CYP3A4 inhibitor for signs of respiratory depression for an extended period of time and adjust the dosage if warranted [see Boxed Warning and Warnings and Precautions (5. 10), and Drug Interactions (7.2)].
  CYP3A4 Inducers
  Co-administration with agents that induce CYP3A4 activity may reduce the efficacy of fentanyl transdermal system.

NONCLINICAL TOXICOLOGY SECTION

13.1 Carcinogenesis, Mutagenesis, and Impairment of Fertility

Carcinogenesis

In a two-year carcinogenicity study conducted in rats, fentanyl was not associated with an increased incidence of tumors at subcutaneous doses up to 33 mcg/kg/day in males or 100 mcg/kg/day in females (0.16 and 0.39 times the human daily exposure obtained via the 100 mcg/h patch based on AUC0-24h comparison).

Mutagenesis

There was no evidence of mutagenicity in the Ames Salmonella mutagenicity assay, the primary rat hepatocyte unscheduled DNA synthesis assay, the BALB/c 3T3 transformation test, and the human lymphocyte and CHO chromosomal aberration in vitro assays.

Impairment of Fertility

The potential effects of fentanyl on male and female fertility were examined in the rat model via two separate experiments. In the male fertility study, male rats were treated with fentanyl (0, 0.025, 0.1 or 0.4 mg/kg/day) via continuous intravenous infusion for 28 days prior to mating; female rats were not treated. In the female fertility study, female rats were treated with fentanyl (0, 0.025, 0.1 or 0.4 mg/kg/day) via continuous intravenous infusion for 14 days prior to mating until day 16 of pregnancy; male rats were not treated. Analysis of fertility parameters in both studies indicated that an intravenous dose of fentanyl up to 0.4 mg/kg/day to either the male or the female alone produced no effects on fertility (this dose is approximately 1.6 times the daily human dose administered by a 100 mcg/h patch on a mg/m2 basis). In a separate study, a single daily bolus dose of fentanyl was shown to impair fertility in rats when given in intravenous doses of 0.3 times the human dose for a period of 12 days.

CLINICAL STUDIES SECTION

Fentanyl transdermal system as therapy for pain due to cancer has been studied in 153 patients. In this patient population, fentanyl transdermal system has been administered in doses of 25 mcg/h to 600 mcg/h. Individual patients have used fentanyl transdermal system continuously for up to 866 days. At one month after initiation of fentanyl transdermal system therapy, patients generally reported lower pain intensity scores as compared to a prestudy analgesic regimen of oral morphine.

The duration of fentanyl transdermal system use varied in cancer patients; 56% of patients used fentanyl transdermal system for over 30 days, 28% continued treatment for more than 4 months, and 10% used fentanyl transdermal system for more than 1 year.

In the pediatric population, the safety of fentanyl transdermal system has been evaluated in 289 patients with chronic pain 2 to 18 years of age. The duration of fentanyl transdermal system use varied; 20% of pediatric patients were treated for ≤ 15 days; 46% for 16 to 30 days; 16% for 31 to 60 days; and 17% for at least 61 days. Twenty-five patients were treated with fentanyl transdermal system for at least 4 months and 9 patients for more than 9 months.

SPL MEDGUIDE SECTION

- Medication Guide
  Fentanyl Transdermal System, Cll
  (fen' ta nil)
  Fentanyl transdermal system is:
  - A strong prescription pain medicine that contains an opioid (narcotic) that is used to manage pain severe enough to require daily around-the-clock, long-term treatment with an opioid, in people who are already regularly using opioid pain medicine, when other pain treatments such as non-opioid pain medicines or immediate-release opioid medicines do not treat your pain well enough or you cannot tolerate them.
  - A long-acting (extended-release) opioid pain medicine that can put you at risk for overdose and death. Even if you take your dose correctly as prescribed you are at risk for opioid addiction, abuse, and misuse that can lead to death.
  - Not for use to treat pain that is not around-the-clock.
  Important information about fentanyl transdermal system:
  - Get emergency help right away if you use too much fentanyl transdermal system (overdose). When you first start taking fentanyl transdermal system, when your dose is changed, or if you take too much (overdose), serious or life threatening breathing problems that can lead to death may occur.
  - Never give anyone else your fentanyl transdermal system. They could die from using it. Store fentanyl transdermal system away from children and in a safe place to prevent stealing or abuse. Selling or giving away fentanyl transdermal system is against the law.
  - If the patch accidentally sticks to a family member while in close contact, take the patch off, wash the area with water, and get emergency help right away because an accidental exposure to fentanyl transdermal system can lead to death or other serious medical problems.
  - Proper disposal of fentanyl transdermal system after use and for unused patches when no longer needed: Fold the sticky sides of the patch together and flush down the toilet. Do not put patches in a trash can.
  Do not use fentanyl transdermal system if you have:
  - severe asthma, trouble breathing, or other lung problems.
  - a bowel blockage or have narrowing of the stomach or intestines.
  Before applying fentanyl transdermal system, tell your healthcare provider if you have a history of:
  - head injury, seizures
  - liver, kidney, thyroid problems
  - problems urinating
  - pancreas or gallbladder problems
  - abuse of street or prescription drugs, alcohol addiction, or mental health problems.
  Tell your healthcare provider if you:
  - have a fever
  - are pregnant or planning to become pregnant. Prolonged use of fentanyl transdermal system during pregnancy can cause withdrawal symptoms in your newborn baby that could be life-threatening if not recognized and treated.
  - are breastfeeding. Fentanyl transdermal system passes into breast milk and may harm your baby.
  - are taking prescription or over-the-counter medicines, vitamins, or herbal supplements. Taking fentanyl transdermal system with certain other medicines can cause serious side effects that could lead to death.
  When using fentanyl transdermal system:
  - Do not change your dose. Apply fentanyl transdermal system exactly as prescribed by your healthcare provider.
  - See the detailed Instructions for Use for information about how to apply and dispose of the fentanyl transdermal system patch.
  - Do not apply more than 1 patch at the same time unless your healthcare provider tells you to.
  - You should wear the fentanyl transdermal patch continuously for 3 days, unless advised otherwise by your healthcare provider.
  - Call your healthcare provider if the dose you are using does not control your pain.
  - Do not stop using fentanyl transdermal system without talking to your healthcare provider.
  While using fentanyl transdermal system DO NOT:
  - Take hot baths or sunbathe, use hot tubs, saunas, heating pads, electric blankets, heated waterbeds, or tanning lamps, or engage in exercise that increases your body temperature. These can cause an overdose that can lead to death.
  - Drive or operate heavy machinery, until you know how fentanyl transdermal system affects you. Fentanyl transdermal system can make you sleepy, dizzy, or lightheaded.
  - Drink alcohol or use prescription or over-the-counter medicines that contain alcohol. Using products containing alcohol during treatment with fentanyl transdermal system may cause you to overdose and die.
  - Wear this fentanyl transdermal system during any magnetic resonance imaging (MRI) procedures to avoid possible burns.
  The possible side effects of fentanyl transdermal system are:
  - constipation, nausea, sleepiness, vomiting, tiredness, headache, dizziness, abdominal pain, itching, redness, or rash where the patch is applied. Call your healthcare provider if you have any of these symptoms and they are severe.
  Get emergency medical help if you have:
  - trouble breathing, shortness of breath, fast heartbeat, chest pain, swelling of your face, tongue or throat, extreme drowsiness, light-headedness when changing positions, or you are feeling faint.
  These are not all the possible side effects of fentanyl transdermal system. Call your doctor for medical advice about side effects. You may report side effects to FDA at 1-800-FDA-1088. For more information go to dailymed.nlm.nih.gov
  Manufactured by:
  Aveva Drug Delivery Systems, Inc., Miramar, FL 33025;
  Manufactured for:
  Apotex Corp., Weston, FL 33326, drugsafety@apotex.com or call
  1-888-333-6127, 9 A.M. to 5 P.M., Eastern Time, Monday through Friday.
  This Medication Guide has been approved by the U.S. FDA.
  Issue: May 2014